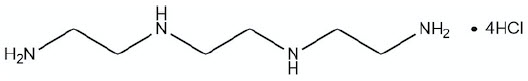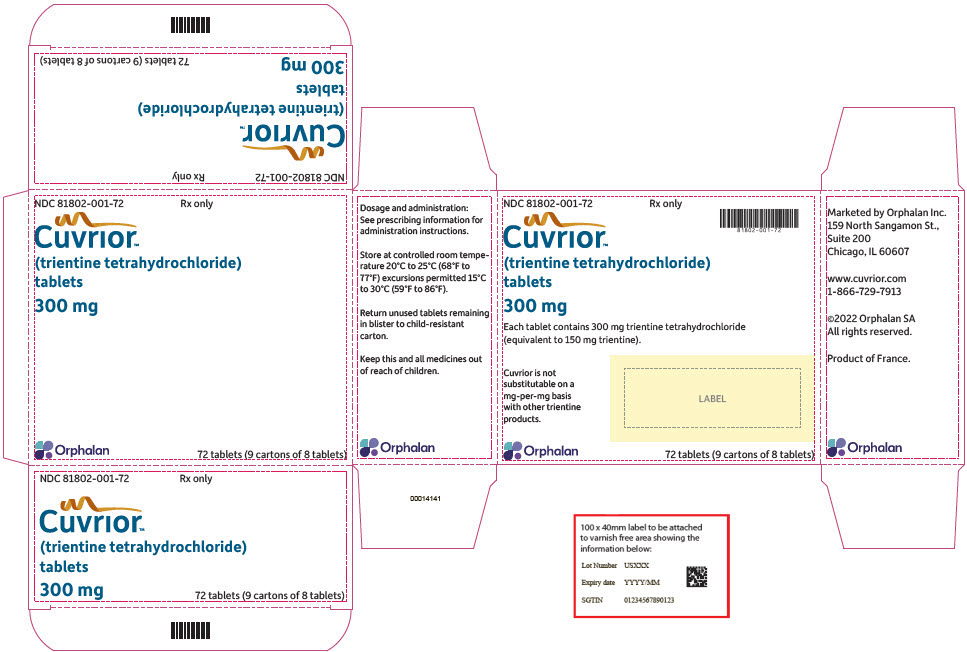 DRUG LABEL: CUVRIOR
NDC: 81802-001 | Form: TABLET, FILM COATED
Manufacturer: Orphalan SA
Category: prescription | Type: HUMAN PRESCRIPTION DRUG LABEL
Date: 20250619

ACTIVE INGREDIENTS: TRIENTINE TETRAHYDROCHLORIDE 300 mg/1 1
INACTIVE INGREDIENTS: MANNITOL; SILICON DIOXIDE; GLYCERYL DIBEHENATE

HIGHLIGHTS OF PRESCRIBING INFORMATION

These highlights do not include all the information needed to use CUVRIOR safely and effectively. See full prescribing information for CUVRIOR.
CUVRIOR® (trientine tetrahydrochloride) tablets, for oral use
Initial U.S. Approval: 1985

1 INDICATIONS AND USAGE

CUVRIOR is a copper chelator indicated for the treatment of adult patients with stable Wilson's disease who are de-coppered and tolerant to penicillamine. (1)

2 DOSAGE AND ADMINISTRATION

Recommended Dosage and Administration

- Starting total daily dosage of CUVRIOR in adults is 300 mg up to 3,000 mg orally in divided doses (2 times daily). See full prescribing information for recommended conversion table when switching from penicillamine to CUVRIOR. (2.1)
- Total daily dosage of CUVRIOR should not exceed 3,000 mg. (2.1)
- If the number of CUVRIOR tablets prescribed per day cannot be equally divided among doses, then divide total daily dosage such that the higher number of tablets is taken with the first daily dose. (2.1)
- Take CUVRIOR on an empty stomach. (2.2)
- Swallow tablets without crushing, chewing, or dissolving tablets. (2.2)

Switching from Other Trientine Products

- CUVRIOR is not substitutable on a milligram-per-milligram basis with other trientine products. (2.3)
- See full prescribing information for additional information on switching from other trientine products. (2.3)

Clinical Monitoring and Laboratory Monitoring of Copper

- Adjust CUVRIOR dosage according to clinical assessment and laboratory monitoring of copper. (2.4)
- See full prescribing information for monitoring recommendations. (2.4)

3 DOSAGE FORMS AND STRENGTHS

Tablets: 300 mg of trientine tetrahydrochloride, functionally scored. (3)

4 CONTRAINDICATIONS

Hypersensitivity to trientine or to any of the excipients in CUVRIOR. (4)

5 WARNINGS AND PRECAUTIONS

- Potential for Worsening of Clinical Symptoms at Initiation of Therapy: May include neurological deterioration. Adjust dosage or discontinue CUVRIOR if clinical condition worsens. (5.1)
- Copper Deficiency: Periodic monitoring is required. (5.2)
- Iron Deficiency: If iron deficiency develops, a short course of iron supplementation may be given. (5.3, 7.1)
- Hypersensitivity Reactions: If rash or other hypersensitivity reaction occurs, consider discontinuing CUVRIOR. (5.4)

6 ADVERSE REACTIONS

Most common adverse reactions (>5%) are abdominal pain, change of bowel habits, rash, alopecia, and mood swings. (6.1)

To report SUSPECTED ADVERSE REACTIONS, contact Orphalan at 1-800-961-8320 or FDA at 1-800-FDA-1088 or www.fda.gov/medwatch.

7 DRUG INTERACTIONS

- Mineral Supplements (e.g. iron, zinc, calcium, magnesium): Avoid concomitant use. If concomitant use is unavoidable (2.2, 7.1):
  - Iron: Take CUVRIOR at least 2 hours before or 2 hours after iron.
  - Other Mineral Supplements: Take CUVRIOR at least 1 hour before or 2 hours after other mineral supplements.
- Other Drugs for Oral Administration: Take CUVRIOR at least 1 hour apart from any other oral drug. (2.2, 7.1)

FULL PRESCRIBING INFORMATION

1 INDICATIONS AND USAGE

CUVRIOR is indicated for the treatment of adult patients with stable Wilson's disease who are de-coppered and tolerant to penicillamine.

2 DOSAGE AND ADMINISTRATION

2.1 Recommended Dosage and Administration

The recommended starting total daily dosage of CUVRIOR in adult patients is 300 mg up to 3,000 mg taken orally in divided doses (two times daily). Table 1 provides the recommended starting total daily dosage of CUVRIOR in adult patients switching from penicillamine to CUVRIOR [see Clinical Studies (14)]. Discontinue penicillamine before starting CUVRIOR.

Table 1: Recommended Starting Total Daily Dosage of CUVRIOR when Switching from Penicillamine to CUVRIOR
Penicillamine Total Daily Dosage | CUVRIOR Starting Total Daily Dosage
125 mg | 300 mg
250 mg | 600 mg
375 mg | 900 mg
500 mg | 900 mg
625 mg | 1,200 mg
750 mg | 1,500 mg
875 mg | 1,800 mg
1,000 mg | 2,100 mg
1,125 mg | 2,400 mg
1,250 mg | 2,400 mg
1,375 mg | 2,700 mg
1,500 mg or greater | 3,000 mg

Adjust the total daily dosage of CUVRIOR according to clinical assessment and laboratory monitoring of copper [see Dosage and Administration (2.4)]. The total daily dosage of CUVRIOR should not exceed 3,000 mg.

If the number of CUVRIOR tablets prescribed per day cannot be equally divided among doses, then divide the total daily dosage such that the higher number of tablets is administered with the first daily dose. Table 2 provides the recommended approach to administration of CUVRIOR tablets to achieve the total daily dosage.

Table 2: Recommended Administration Schedule of CUVRIOR Tablets to Achieve Total Daily Dosage
CUVRIOR | Number of CUVRIOR Tablets to Administer
Total Daily Dosage | Morning | Evening
300 mg | 1 | 0
600 mg | 1 | 1
900 mg | 2 | 1
1,200 mg | 2 | 2
1,500 mg | 3 | 2
1,800 mg | 3 | 3
2,100 mg | 4 | 3
2,400 mg | 4 | 4
2,700 mg | 5 | 4
3,000 mg | 5 | 5

2.2 Important Administration Instructions

- Discontinue penicillamine before starting CUVRIOR [see Dosage and Administration (2.1)].
- Administer CUVRIOR on an empty stomach, at least 1 hour before meals or 2 hours after meals and at least 1 hour apart from any other food or milk.
- Avoid concomitant use of mineral supplements (e.g. iron, zinc, calcium, magnesium). If concomitant use of mineral supplements is unavoidable [see Drug Interactions (7.1)]:
  - Iron supplements: Administer CUVRIOR at least 2 hours before or 2 hours after administration of an iron supplement.
  - Other mineral supplements: Administer CUVRIOR at least 1 hour before or 2 hours after administration of other mineral supplements.
- Administer CUVRIOR at least 1 hour apart from any other oral drug.
- Do not remove tablets from the blister pack until just before dosing.
- Swallow tablets of CUVRIOR without crushing, chewing, or dissolving tablets. For patients who have difficulty swallowing the tablet whole, the scored tablet can be divided into two equal halves. Do not store the tablet for future use after the blister has been opened.
- Avoid the use of CUVRIOR in patients who are unable to swallow tablets.

2.3 Switching to CUVRIOR from Other Trientine Products

CUVRIOR is not substitutable on a milligram-per-milligram basis with other trientine products.

If switching a patient from a trientine hydrochloride formulation to CUVRIOR, note that the content of the active moiety (trientine base) is not the same as CUVRIOR. A 250 mg capsule of trientine hydrochloride contains 167 mg of trientine base; in contrast, each 300 mg tablet of CUVRIOR contains 150 mg of trientine base [see Clinical Pharmacology (12.3)].

2.4 Clinical Monitoring and Laboratory Monitoring of Copper

Adjust the total daily dosage of CUVRIOR according to clinical assessment and serum non-ceruloplasmin copper (NCC) levels. Evaluate serum NCC levels when initiating CUVRIOR treatment, after 3 months of treatment and approximately every 6 months thereafter. Therapy may also be monitored periodically (every 6 to 12 months) with measurement of 24-hour urinary copper excretion (UCE) [see Warnings and Precautions (5.1, 5.2)].

3 DOSAGE FORMS AND STRENGTHS

Tablets: 300 mg of trientine tetrahydrochloride (equivalent to 150 mg of trientine), oblong, yellow coated, functionally scored, printed with OL75 on each side of score line in black ink. Each large carton contains nine small cartons, each containing a blister pack of 8 tablets (a total of 72 tablets in the large carton).

4 CONTRAINDICATIONS

CUVRIOR is contraindicated in patients with hypersensitivity to trientine or to any of the excipients in CUVRIOR [see Warnings and Precautions (5.4)].

5 WARNINGS AND PRECAUTIONS

5.1 Potential for Worsening of Clinical Symptoms at Initiation of Therapy

Worsening of clinical symptoms, including neurological deterioration, may occur at the beginning of CUVRIOR therapy due to mobilization of excess stores of copper. Adjust the dosage or discontinue CUVRIOR if the patient's clinical condition worsens.

Evaluate serum non-ceruloplasmin copper (NCC) levels when initiating CUVRIOR treatment, after 3 months of treatment and approximately every 6 months thereafter. Therapy may also be monitored periodically (every 6 to 12 months) with measurement of 24-hour urinary copper excretion (UCE) [see Dosage and Administration (2.4)].

5.2 Copper Deficiency

Copper deficiency may develop following treatment with CUVRIOR. Close monitoring for manifestations of copper deficiency is required particularly when copper requirements may change, such as in pregnancy, where appropriate control of copper levels are required to ensure proper growth and mental development [see Dosage and Administration (2.4) and Use in Specific Populations (8.1)].

5.3 Iron Deficiency

Iron deficiency may develop following treatment with CUVRIOR, especially in menstruating or pregnant women, or as a result of the low copper diet recommended for Wilson's disease. If necessary, iron may be given in short courses, but at least two hours should elapse between administration of CUVRIOR and iron [see Drug Interactions (7.1) and Use in Specific Populations (8.1)].

5.4 Hypersensitivity Reactions

Hypersensitivity reactions, characterized by rash, have been reported with the use of trientine. In Trial 1, rash was reported in 12% (3/26) of CUVRIOR-treated patients, and one of these patients discontinued CUVRIOR because of the rash [see Adverse Reactions (6.1)]. If a patient develops a rash or other hypersensitivity reaction during treatment with CUVRIOR, assess clinically and consider discontinuing CUVRIOR [see Contraindications (4)].

6 ADVERSE REACTIONS

The following clinically significant adverse reactions are described elsewhere in the labeling:

- Potential for Worsening of Clinical Symptoms at Initiation of Therapy [see Warnings and Precautions (5.1)]
- Copper Deficiency [see Warnings and Precautions (5.2)]
- Iron Deficiency [see Warnings and Precautions (5.3)]
- Hypersensitivity Reactions [see Warnings and Precautions (5.4)]

6.1 Clinical Trials Experience

Because clinical trials are conducted under widely varying conditions, adverse reaction rates observed in the clinical trials of a drug cannot be directly compared to rates in the clinical trials of another drug and may not reflect the rates observed in practice.

Common Adverse Reactions

Table 3 presents common adverse reactions over a 24-week period from Trial 1, a prospective, randomized, multi-center study that was conducted in adult patients with Wilson's disease who were de-coppered and tolerant to penicillamine [see Clinical Studies (14)]. Patients were either switched to receive CUVRIOR (N=26) or continued to receive penicillamine (N=27).

Table 3: Common Adverse Reactions [Adverse reactions that occurred in >5% of CUVRIOR-treated patients and greater than in patients who continued to receive penicillamine.] from a Clinical Study of CUVRIOR in Adult Patients with Wilson's Disease (Trial 1)
Adverse Reaction | CUVRIOR (N=26) n (%) | Penicillamine (N=27) n (%)
Abdominal pain [Abdominal pain is composed of several similar terms] | 5 (19%) | 1 (4%)
Change of bowel habits [Includes constipation, abnormal feces, soft feces] | 4 (15%) | 0
Rash [Rash is composed of several similar terms] | 3 (12%) | 0
Alopecia | 2 (8%) | 1 (4%)
Mood swings | 2 (8%) | 0

Other Adverse Reactions

In Trial 1, anemia developed in 4% (1/26) of CUVRIOR-treated patients and in no patients who continued to receive penicillamine.

In addition, the following adverse reactions have been reported in clinical studies of patients with Wilson's disease who were on therapy with trientine hydrochloride:

- Metabolism and Nutrition Disorders: Iron deficiency
- Musculoskeletal and Connective Tissue Disorders: Systemic lupus erythematosus

6.2 Postmarketing Experience

The following adverse reactions have been identified during postapproval use of trientine hydrochloride. Because these reactions are reported voluntarily from a population of uncertain size, it is not always possible to reliably estimate their frequency or establish a causal relationship to drug exposure:

- Gastrointestinal Disorders: Colitis
- Musculoskeletal and Connective Tissue Disorders: Muscle spasms, Rhabdomyolysis
- Nervous System Disorders: Dystonia, Myasthenia gravis

7 DRUG INTERACTIONS

7.1 Mineral Supplements and Other Oral Drugs

CUVRIOR has the potential to chelate non-copper cations in mineral supplements and other oral drugs, and could be rendered ineffective prior to systemic absorption.

Mineral Supplements

Avoid concomitant use of mineral supplements such as iron, zinc, calcium, or magnesium with CUVRIOR because they may reduce the absorption of CUVRIOR.

However, if iron deficiency develops [see Warnings and Precautions (5.3)], iron supplementation may be given in short courses, but because iron and CUVRIOR each inhibit absorption of the other, administer CUVRIOR at least 2 hours before or 2 hours after administration of an iron supplement [see Dosage and Administration (2.2)].

If concomitant use of other mineral supplements is unavoidable, administer CUVRIOR at least 1 hour before or 2 hours after administration of other mineral supplements.

Other Drugs for Oral Administration

Administer CUVRIOR at least 1 hour apart from any other oral drug.

8 USE IN SPECIFIC POPULATIONS

8.1 Pregnancy

Risk Summary

Available data from published literature and postmarketing experience over several decades with use of trientine for the treatment of Wilson's disease have not identified any drug-associated risks for major birth defects, miscarriages, or other adverse maternal or fetal outcomes. Untreated Wilson's disease may result in worsening disease symptoms during pregnancy and increase the risk of miscarriages in some symptomatic patients (see Clinical Considerations).

In animal reproduction studies, oral administration of trientine in rats during organogenesis resulted in increased embryo-fetal loss at a dose lower than the maximum recommended dose and produced fetal abnormalities at 2.7 times the maximum recommended dose. Copper supplementation in pregnant rats produced a marked reduction in trientine-induced fetal abnormalities. Oral administration of trientine dihydrochloride to pregnant mice during organogenesis increased the percentage of mice with total embryo-fetal loss at approximately 4.3 times the maximum recommended dose and produced fetal abnormalities at approximately 1.1 times the maximum recommended dose. The mechanism of embryo-fetal harm (e.g., copper depletion) was not determined in the mouse study [see Warnings and Precautions (5.2) and Data].

Monitor copper levels throughout pregnancy and use the minimum effective dosage of CUVRIOR throughout pregnancy.

The estimated background risk of major birth defects and miscarriage for the indicated populations is unknown. All pregnancies have a background risk of birth defect, loss, or other adverse outcomes. In the U.S. general population, the estimated background risk of major birth defects and miscarriage in clinically recognized pregnancies is 2 to 4% and 15 to 20%, respectively.

Clinical Considerations

Disease-Associated Maternal and/or Embryo/Fetal Risk

Untreated Wilson's disease or discontinuation of treatment during pregnancy may result in worsening neurological and hepatic symptoms, including rare reports of hepatic decompensation and liver failure. Untreated Wilson's disease may also increase the risk of miscarriage in some symptomatic patients. Increased copper deposition in the placenta and fetal liver may adversely impact the fetus.

Maternal Adverse Reactions

Trientine may chelate non-copper cations (e.g., iron, calcium). Maintain appropriate levels during pregnancy [see Dosage and Administration (2.2), Warnings and Precautions (5.2, 5.3), and Drug Interactions (7.1)].

Fetal/Neonatal Adverse Reactions

Chelator-induced copper deficiency may have adverse effects on the fetus.

Data

Animal Data

In embryo-fetal development studies in rats, trientine was administered orally at doses up to approximately 835 mg/kg/day during organogenesis. An increased incidence of resorptions was observed at a dose lower than the maximum recommended dose (1,500 mg/day trientine free base equivalent), based on body surface area. An increased incidence of fetal abnormalities, including hemorrhage and edema, was observed at 2.7 times the maximum recommended dose, based on body surface area. When pregnant rats were treated with trientine and supplemented with copper (concentration of 50 mcg/g in the diet), fetal abnormalities were markedly reduced, indicating that the mechanism of embryo-fetal harm in rats with no copper supplementation was based on copper depletion (primary pharmacology of trientine).

In embryo-fetal development studies in mice, trientine dihydrochloride was administered orally at doses up to approximately 2,000 mg/kg/day during organogenesis. A dose-dependent increase in the incidence of abnormal fetuses occurred at all doses. Fetal abnormalities included hemorrhages and delayed ossification which were observed starting at 500 mg/kg/day, microcephaly and hydrocephaly starting at 1,000 mg/kg/day, and exencephaly at 2,000 mg/kg/day (the doses were 1.1, 2.1, and 4.3 times the maximum recommended dose, respectively, based on body surface area). The percentage of dams with total resorption was increased at 2,000 mg/kg/day (5.3 times the maximum recommended dose based on body surface area). The mechanism of embryo-fetal harm (e.g. copper depletion) was not determined in this study.

8.2 Lactation

Risk Summary

The available published data are inconsistent regarding the detection of trientine in breastmilk. Available published literature have not reported drug-associated adverse effects in infants exposed to trientine through breastmilk. There are no data on the effects of trientine on milk production. The developmental and health benefits of breastfeeding should be considered along with the mother's clinical need for CUVRIOR and any potential adverse effects on the breastfed infant from CUVRIOR or from the underlying condition.

8.4 Pediatric Use

The safety and effectiveness of CUVRIOR in pediatric patients have not been established.

8.5 Geriatric Use

In Trial 1, of the total number of CUVRIOR-treated patients, 1 (4%) was 65 years of age and older [see Clinical Studies (14)]. Clinical studies with trientine did not include sufficient numbers of patients aged 65 and over to determine whether they respond differently from younger adult patients. Other reported clinical experience with trientine is insufficient to determine differences in responses between geriatric and younger adult patients. In general, dose selection should be cautious, usually starting at the low end of the dosing range, reflecting the greater frequency of decreased hepatic, renal, or cardiac function, and of concomitant disease or other drug therapy.

10 OVERDOSAGE

Occasional cases of trientine overdose have been reported. A large overdose of 60 g of trientine hydrochloride (equivalent to 80 g CUVRIOR) resulted in nausea, vomiting, dizziness, mild acute kidney injury, mild hypophosphatemia, low serum zinc, and low serum copper. The patient recovered following intravenous hydration and supportive measures.

There is no antidote for trientine acute overdose.

Chronic use of trientine hydrochloride at dosages above the maximum recommended dosage has resulted in sideroblastic anemia.

11 DESCRIPTION

CUVRIOR contains trientine tetrahydrochloride which is a salt of trientine, a copper chelator. The structural formula of trientine tetrahydrochloride is:

Molecular Formula | C6H22Cl4N4
Molecular Weight | 292.08 g mol^-1

CUVRIOR (trientine tetrahydrochloride) tablets are for oral administration and contain 300 mg of trientine tetrahydrochloride (equivalent to 150 mg trientine). Tablets include the following inactive ingredients: colloidal silicon dioxide, glyceryl dibehenate, and mannitol. The film coating comprises ferric oxide yellow, glyceryl monocaprylocaprate (Type I), polyvinyl alcohol, purified talc, sodium lauryl sulfate, and titanium dioxide.

12 CLINICAL PHARMACOLOGY

12.1 Mechanism of Action

Trientine, a copper chelator, eliminates absorbed copper from the body by forming a stable complex that is then eliminated through urinary excretion. Trientine also chelates copper in the intestinal tract, reducing copper absorption.

12.2 Pharmacodynamics

In Trial 1, serum non-ceruloplasmin copper (NCC) and 24-hour urinary copper excretion (UCE) were measured in adult patients with Wilson's disease who were de-coppered and tolerating penicillamine and who had switched to CUVRIOR. In patients who had switched to CUVRIOR, mean UCE decreased over time (see Table 4). On the other hand, the mean serum NCC in patients who had switched to CUVRIOR was comparable to the mean serum NCC in patients who remained on penicillamine [see Clinical Studies (14)].

Table 4: Mean Serum NCC and 24-Hour UCE Over Time by Initial Total Daily Dosage of CUVRIOR at Week 12 in Trial 1
 | < 900 mg N=3 |  | 900 mg to 1,800 mg N=9 |  | 1,800 mg to 3,600 mg [One out of 14 patients received 3,600 mg (1.2 times the highest recommended total daily dosage)] N=14
Visit | Serum NCC (mcg/L) | 24-hour UCE (mcg/24h) | Serum NCC (mcg/L) | 24-hour UCE (mcg/24h) | Serum NCC (mcg/L) | 24-hour UCE (mcg/24h)
Week 12 [At Week 12, patients who were adequately controlled and tolerating penicillamine and who switched to CUVRIOR] | 93.1 (78.2) | 438.0 (219.0) | 70.8 (20.3) [N=8] | 455.3 (283.4) | 62 .0 (25.2) | 612.8 (320.1) [N=13]
Week 24 | 59.3 (32.5) [N=2] | 312.5 (174.7) | 63.9 (19.6) | 223.8 (134.3) | 58.0 (15.6) [N=12] | 340.9 (160.9)
Week 36 | 100.3 (81.8) | 425.6 (324.7) | 49.1 (12.3) | 267.8 (258.2) | 53.9 (9.6) | 274.0 (144.8)
NCC = non-ceruloplasmin copper (measured by an assay not commercially available); UCE = urinary copper excretion. Standard deviations are shown in parentheses.

12.3 Pharmacokinetics

Absorption

The pharmacokinetic profile has been evaluated in healthy subjects following single oral administration of up to 1,500 mg CUVRIOR under fasting conditions.

The median time to the peak concentration (Tmax) of trientine ranged from 1.25 to 2 hours. Mean (± standard deviation) maximum plasma concentrations (Cmax) after 900 mg and 1,500 mg CUVRIOR were 2030±981, and 3430±1480 ng/mL, respectively. The systemic exposure (AUC) of trientine increased in a dose proportional manner over the range of 900 mg to 1,500 mg (mean AUCinf of 9750±4910 and 17200±9470 ng∙h/mL, respectively).

After administration of 900 mg (3 tablets) of CUVRIOR, the mean AUC was 11% lower compared to 750 mg (3 capsules) of trientine hydrochloride. After administration of 1,500 mg (5 tablets) of CUVRIOR, the mean AUC was comparable to 1,250 mg (5 capsules) of trientine hydrochloride [see Dosage and Administration (2.3)].

Elimination

The mean terminal half-life (t1/2) of trientine ranged from 13.8 to 16.5 hours.

Metabolism

Trientine is acetylated into two major active metabolites, N(1)-acetyltriethylenetetramine (MAT) and N(1),N(10)-diacetyltriethylenetetramine (DAT).

After the administration of a 900 mg dose of CUVRIOR, mean Cmax of MAT and DAT respectively were 1450±471 and 500±467 ng/mL and mean AUCinf was 15400±4200 and 5970±3390 ng∙h/mL. Mean T1/2 was 17.1±9.22 and 14.7±8.39 hours for MAT and DAT, respectively.

After the administration of a 1,500 mg dose of CUVRIOR, mean Cmax of MAT and DAT respectively were 2050±596 and 683±632 ng/mL and mean AUCinf was 22000±5770 and 7690±3970 ng∙h/mL. Mean T1/2 was 19.3±12.3 and 11.2±3.30 hours for MAT and DAT, respectively.

Excretion

Trientine and its metabolites are excreted in the urine.

Specific Populations

Male and Female Patients

Following a single oral dose of 900 mg CUVRIOR, the systemic exposures (Cmax and AUCinf) were similar between males and females, although males appeared to have higher systemic exposures of trientine (approximately 30% and 50% higher for Cmax and AUCinf, respectively) following a single oral dose of 1,500 mg of CUVRIOR. This difference is not considered clinically meaningful for CUVRIOR.

13 NONCLINICAL TOXICOLOGY

13.1 Carcinogenesis, Mutagenesis, Impairment of Fertility

Carcinogenesis

Oral carcinogenicity studies have not been conducted with trientine.

Mutagenesis

Trientine was positive in the bacterial reverse mutation (Ames) assay, the in vitro unscheduled DNA synthesis assay in rat hepatocytes, and the sister-chromatid exchange assay in Chinese hamster ovary (CHO) cells. Trientine was negative in the HGPRT gene mutation assay in CHO cells and the in vivo mouse micronucleus assay.

Impairment of Fertility

Fertility studies have not been conducted with trientine.

13.2 Animal Toxicology and/or Pharmacology

Severe pulmonary toxicity occurred in a 26-week oral toxicity study of trientine dihydrochloride in rats. However, the relevance of this finding to safety risk in patients with Wilson's disease is unknown. Deaths related to pulmonary injury occurred in male rats at 175 and 600 mg/kg/day (1/12 and 3/20 males, respectively). Pulmonary lesions were observed in male rats at 50 mg/kg/day (lower than the maximum recommended dose [1,500 mg/day trientine free base equivalent] based on body surface area). In female rats, pulmonary lesions occurred at 175 mg/kg/day (lower than the maximum recommended dose based on body surface area). Pulmonary toxicity was dose-dependent in both sexes. The lesions included alveolar fibrosis, bronchiolar hyperplasia/ epithelialization of alveolar wall, focal chronic interstitial pneumonitis, bronchiolar epithelium hypertrophy, alveolar hemorrhage (males only), necrosis/regenerative hyperplasia of terminal bronchioles (males only), and acute interstitial pneumonitis (males only). Most of the pulmonary lesions remained after a 13-week recovery period, and were considered as irreversible (e.g., alveolar fibrosis, bronchiolar hyperplasia/epithelialization of alveolar wall, focal chronic interstitial pneumonitis). Pulmonary toxicity also occurred in a 13-week oral study of trientine dihydrochloride in mice. The effects included interstitial inflammation and alveolar histiocytic infiltration, observed at a dose approximately equal to the maximum recommended dose based on body surface area. The mechanism of pulmonary toxicity was not clearly established as due to copper depletion (primary pharmacology) or due to other drug activity.

Neurological and/or musculoskeletal clinical signs (abnormal "stiff-legged" gait, limited use of limb, underactivity, body tremors) occurred in a 26-week oral toxicity study of trientine dihydrochloride in dogs at 5.5 times the estimated human exposure at the maximum recommended dose (based on AUC). The mechanism for these clinical signs was not clearly established as due to copper depletion (primary pharmacology) or due to other drug activity. Because of the severity of the clinical signs at exposures above 5.5 times the maximum exposure in humans, some dogs were sacrificed for humane reasons after 9 weeks of treatment, and treatment for the remaining animals in the same dose group was stopped after 10 weeks. Neurological and/or musculoskeletal clinical signs were generally not observed at exposures that were 3.4 times the human exposure at the maximum recommended dose.

14 CLINICAL STUDIES

The effectiveness of CUVRIOR for the treatment of adult patients with stable Wilson's disease who are decoppered and tolerant to penicillamine was demonstrated in a phase 3 trial (Trial 1). In addition, the safety and effectiveness of CUVRIOR in Wilson's Disease is further supported by studies of another trientine product in patients intolerant to penicillamine.

Trial 1 was a randomized, active-controlled, multi-center, non-inferiority study (NCT03539952) conducted in 53 adult patients with Wilson's disease. The objective was to compare treatment with CUVRIOR to treatment with penicillamine. All patients had been receiving penicillamine for at least 1 year prior to study entry, were adequately controlled and tolerating penicillamine, and had a serum NCC level between ≥ 25 and ≤ 150 mcg/L.

At the start of the study, patients entered a 12-week baseline period and continued to receive their established total daily dosage of penicillamine for 12 weeks. At Week 12, patients were randomized to either remain on penicillamine (N=27) or to switch to CUVRIOR (N=26) for the 24-week post-randomization period (i.e., Week 12 through Week 36). For patients switching to CUVRIOR, where possible, the initial total daily dosage was determined as the trientine base in mg that was the same as the patient's total daily dosage in mg of penicillamine. Where a direct mg to mg conversion was not possible, the total daily dosage of CUVRIOR was rounded to the nearest 150 mg of trientine base (300 mg trientine tetrahydrochloride salt) to the penicillamine total daily dosage. The dosage was permitted to be adjusted depending on clinical response. The mean CUVRIOR total daily dosage was 1,800 mg. Upon switching from penicillamine to CUVRIOR, 3 patients switched to a CUVRIOR total daily dosage < 900 mg, 9 patients to a total daily dosage between 900 mg and 1,800 mg, and 14 patients to a total daily dosage of 1,800 mg or greater. Three out of 26 patients increased and one patient reduced the total daily dosage across the 24-week post-randomization period.

The results are presented in Table 5. The primary efficacy endpoint was the mean serum non-ceruloplasmin copper (NCC) level at 24 weeks post-randomization (Week 36). At Week 12 (prior to initiation of randomized treatment), the mean (95% CI) NCC levels in the penicillamine and CUVRIOR arms were 77 mcg/L (66; 88) and 66 mcg/L (55; 76), respectively. The mean NCC level at Week 36 as measured using an assay not commercially available was similar in patients receiving CUVRIOR and in patients receiving penicillamine. However, the mean 24-hour urinary copper excretion (UCE) at Week 36 was lower in patients receiving CUVRIOR as compared to patients receiving penicillamine. A decrease in UCE has been observed when switching patients from penicillamine products to trientine products. All patients in both treatment arms were considered clinically stable as determined by an adjudication committee at Week 36.

Table 5: Serum NCC [Measured by an assay not commercially available] and 24-Hour UCE Results at Week 36 in Trial 1
Parameter | Penicillamine Arm (N=27) | CUVRIOR Arm (N=26) | Difference [The difference in mean levels (penicillamine minus CUVRIOR)]
Serum NCC (mcg/L)
Mean [The reported means and treatment effects are based on a general linear model including covariates for site, treatment, visit, and a treatment by visit interaction term.] (95% CI) | 46 (35; 58) | 56 (44; 67) | -9 (-24; 6)
24-hour UCE (mcg/24h)
Mean (95% CI) | 511 (415; 607) | 274 (183; 366) | 236 (111; 361)
CI = confidence interval; NCC = non-ceruloplasmin copper; UCE = urinary copper excretion

16 HOW SUPPLIED/STORAGE AND HANDLING

CUVRIOR tablets, 300 mg of trientine tetrahydrochloride, are oblong, yellow coated, functionally scored, and imprinted with OL75 on each side. Each large carton (NDC 81802-001-72) contains nine child-resistant small cartons (NDC 81802-001-08), each containing a blister pack of 8 tablets (a total of 72 tablets in the large carton). The fewest number of tablets that can be dispensed is 8 tablets in a small carton.

Do not remove tablets from the blister pack until the time of dosing.

STORAGE AND HANDLING

Store at a controlled room temperature of 20°C to 25°C (68°F to 77°F); excursions between 15°C and 30°C (59°F and 86°F) are permitted [see USP Controlled Room Temperature].

17 PATIENT COUNSELING INFORMATION

Administration Instructions

Advise patients or their caretaker(s) to [see Dosage and Administration (2.2)]:

- Take CUVRIOR on an empty stomach (at least 1 hour before meals or 2 hours after meals and at least 1 hour apart from other food or milk).
- Avoid concomitant use of mineral supplements (e.g. iron, zinc, calcium, magnesium). If concomitant use of mineral supplements is unavoidable [see Drug Interactions (7.1)]:
  - Advise patients taking an iron supplement to take CUVRIOR at least 2 hours before or 2 hours after taking an iron supplement.
  - Advise patients taking other mineral supplements to take CUVRIOR at least 1 hour before or 2 hours after taking other mineral supplements.
- Take CUVRIOR at least 1 hour apart from any other oral drug.
- Remove CUVRIOR tablets from the blister pack only at the time of dosing.
- Swallow tablets of CUVRIOR without crushing, chewing, or dissolving tablets. Advise patients that if they have difficulty swallowing the tablet whole, the scored tablet can be divided into two equal halves. Advise patients not to store the tablet for future use after the blister has been opened.

Laboratory Monitoring

Advise patients that copper level monitoring is required periodically during CUVRIOR therapy [see Dosage and Administration (2.4) and Warnings and Precautions (5.1, 5.2)].

Potential for Worsening of Clinical Symptoms at Initiation of Therapy

Advise patients or their caretaker(s) to notify their healthcare provider if they experience worsening of clinical symptoms, including neurological deterioration [see Warnings and Precautions (5.1)].

Copper or Iron Deficiency

Advise patients or their caretaker(s) to notify their healthcare provider if they experience any signs or symptoms of copper or iron deficiency [see Warnings and Precautions (5.2, 5.3)].

Hypersensitivity Reactions

Advise patients or their caretaker(s) to notify their healthcare provider if they develop a rash or other hypersensitivity reaction while taking CUVRIOR [see Warnings and Precautions (5.4)].

Marketed by: Orphalan, Chicago, IL 60607
Product of France
CUVRIOR is a registered trademark of Orphalan SA
©2025 Orphalan SA, all rights reserved.

PRINCIPAL DISPLAY PANEL - 72 Tablet Blister Pack Carton

NDC 81802-001-72
Rx only

Cuvrior™

(trientine tetrahydrochloride)
tablets

300 mg

Orphalan
72 tablets (9 cartons of 8 tablets)